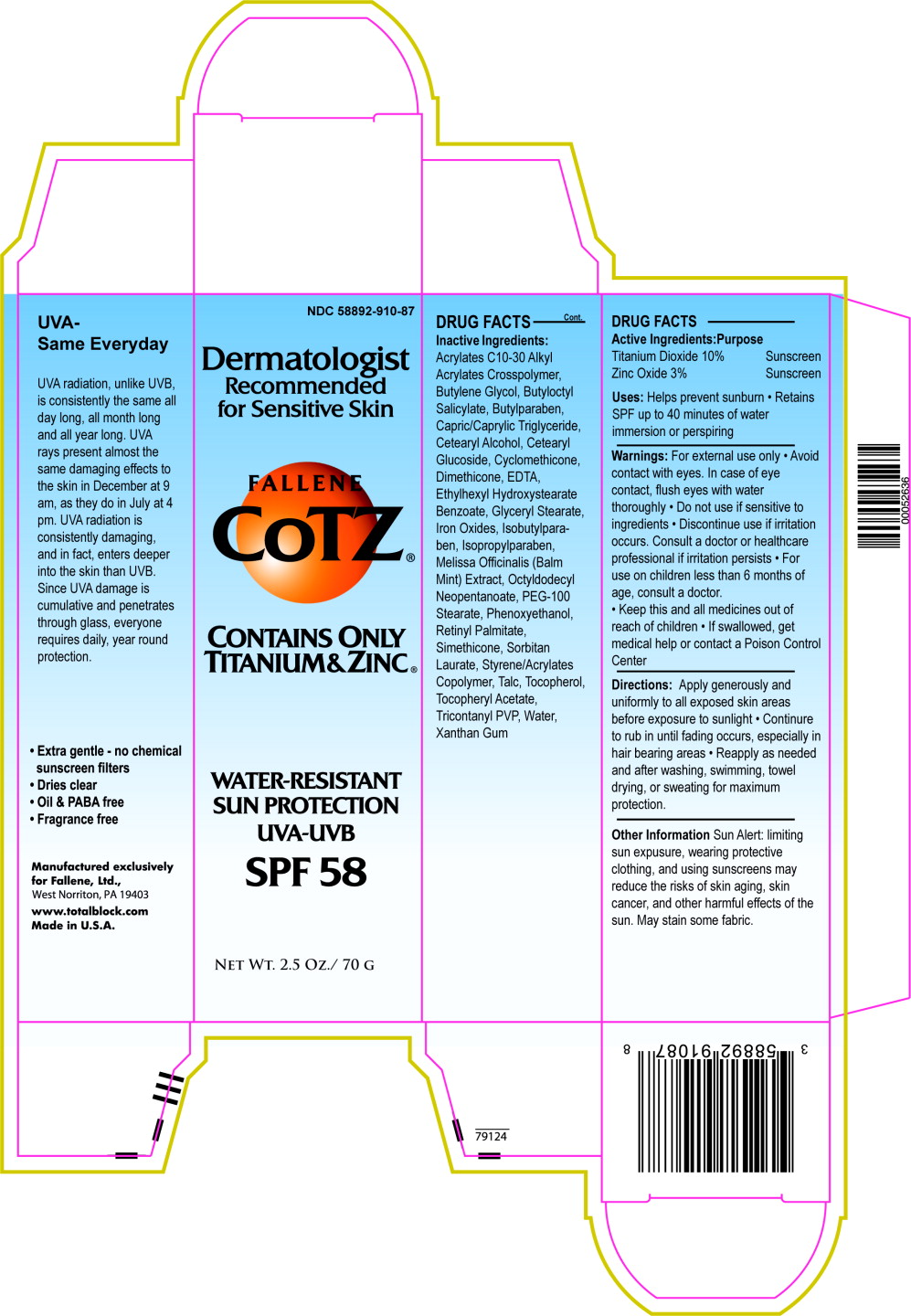 DRUG LABEL: CoTZ SPF 58 
NDC: 58892-910 | Form: CREAM
Manufacturer: Fallien Cosmeceuticals, LTD.
Category: otc | Type: HUMAN OTC DRUG LABEL
Date: 20100804

ACTIVE INGREDIENTS: Titanium Dioxide 100 mg/1 g; Zinc Oxide 30 mg/1 g
INACTIVE INGREDIENTS: Butylene Glycol; Butylparaben; Medium-Chain Triglycerides; Carbomer Copolymer Type B; Cyclomethicone; Dimethicone; Edetate Disodium; Glyceryl Monostearate; Ferric Oxide Yellow; Ferrosoferric Oxide; Isobutylparaben; Isopropylparaben; Lemon Balm Oil; Octyldodecyl Neopentanoate; Polyoxyl 100 Stearate; Phenoxyethanol; Vitamin A Palmitate; Sorbitan Monolaurate; Talc; Alpha-Tocopherol; Alpha-Tocopherol Acetate; Water; Xanthan Gum

FALLENE CoTZ®

DRUG FACTS

Active Ingredients

Titanium Dioxide 10%

Zinc Oxide 3%

Purpose

Sunscreen

Sunscreen

INDICATIONS AND USAGE

Uses: Helps prevent sunburn

- Retains SPF up to 40 minutes of water immersion or perspiring

Warnings: For external use only

- Avoid contact with eyes. In case of eye contact, flush eyes with water thoroughly
- Do not use if sensitive to ingredients • Discontinue use if irritation occurs. Consult a doctor or healthcare professional if irritation persists
- For use on children less than 6 months of age, consult a doctor.
- Keep this and all medicines out of reach of children
- If swallowed, get medical help or contact a Poison Control Center

DOSAGE AND ADMINISTRATION

Directions: Apply generously and uniformly to all exposed skin areas before exposure to sunlight

- Continure to rub in until fading occurs, especially in hair bearing areas
- Reapply as needed and after washing, swimming, towel drying, or sweating for maximum protection.

Other Information Sun Alert: limiting sun expusure, wearing protective clothing, and using sunscreens may reduce the risks of skin aging, skin cancer, and other harmful effects of the sun. May stain some fabric.

Inactive Ingredients

Acrylates C10-30 Alkyl

Acrylates Crosspolymer,

Butylene Glycol, Butyloctyl

Salicylate, Butylparaben,

Capric/Caprylic Triglyceride,

Cetearyl Alcohol, Cetearyl

Glucoside, Cyclomethicone,

Dimethicone, EDTA,

Ethylhexyl Hydroxystearate

Benzoate, Glyceryl Stearate,

Iron Oxides, Isobutylparaben,

Isopropylparaben,

Melissa Officinalis (Balm

Mint) Extract, Octyldodecyl

Neopentanoate, PEG-100

Stearate, Phenoxyethanol,

Retinyl Palmitate,

Simethicone, Sorbitan

Laurate, Styrene/Acrylates

Copolymer, Talc, Tocopherol,

Tocopheryl Acetate,

Tricontanyl PVP, Water,

Xanthan Gum

UVA - Same Everyday

UVA radiation, unlike UVB, is consistently the same all day long, all month long and all year long. UVA rays present almost the same damaging effects to the skin in December at 9 am, as they do in July at 4 pm. UVA radiation is consistently damaging, and in fact, enters deeper into the skin than UVB. Since UVA damage is cumulative and penetrates through glass, everyone requires daily, year round protection.

- Extra gentle - no chemical sunscreen filters
- Dries clear
- Oil & PABA free
- Fragrance free

Manufactured exclusively for:
Fallien, West Norriton, PA 19403
www.totalblock.com

Made in USA

Principal Display Panel – Carton Label

NDC 58892-910-87

Dermatologist Recommended for Sensitive Skin

FALLENE CoTZ®

Contains Only Titanium & Zinc®

WATER-RESISTANT SUN PROTECTION

UVA-UVB SPF 58

Net Wt. 2.5 Oz./ 70 g